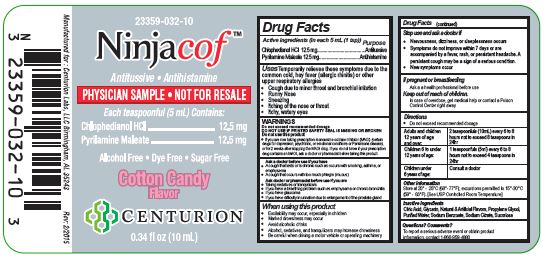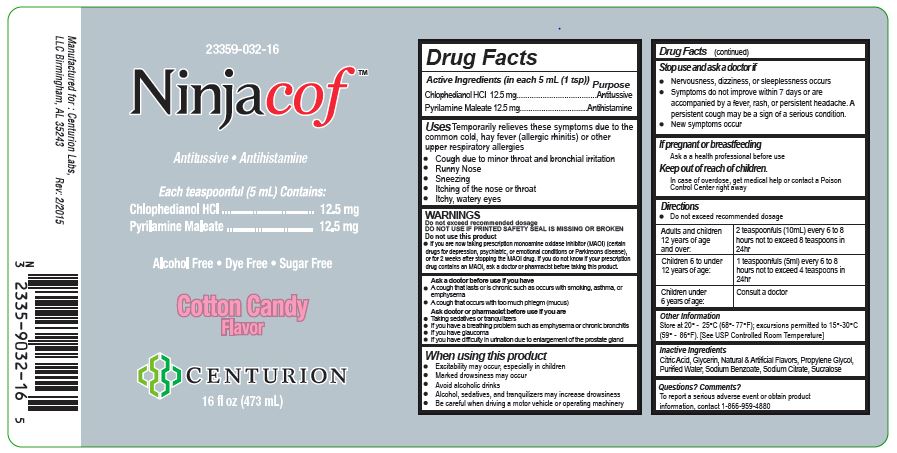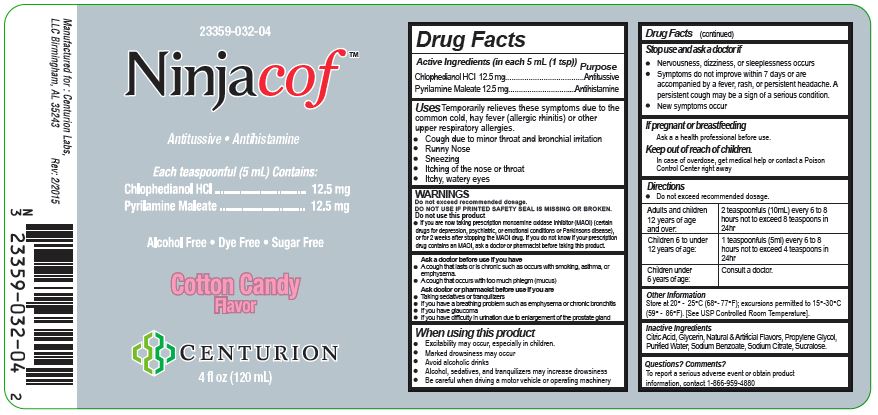 DRUG LABEL: Ninjacof
NDC: 23359-032 | Form: SOLUTION
Manufacturer: Centurion Labs, LLC
Category: otc | Type: HUMAN OTC DRUG LABEL
Date: 20251229

ACTIVE INGREDIENTS: CHLOPHEDIANOL HYDROCHLORIDE 12.5 mg/5 mL; PYRILAMINE MALEATE 12.5 mg/5 mL
INACTIVE INGREDIENTS: ANHYDROUS CITRIC ACID; PROPYLENE GLYCOL; SODIUM BENZOATE; WATER; SODIUM CITRATE; SUCRALOSE; GLYCERIN

Ninjacof

OTC - ACTIVE INGREDIENT SECTION

Active ingredients (in each 5 ml) Purpose
Chlophedianol HCI 12.5 mg ..................................... Antitussive
Pyrilamine Maleate 12.5 mg ................................. Antihistamine

Purpose

Antitussive

Antihistamine

INDICATIONS & USAGE SECTION

Uses Temporarily relieves these symptoms due to the common cold, hay fever (allergic rhinitis) or other upper respiratory allergies:

- cough due to minor throat and bronchial irritation
- calms the cough control center and relieves coughing
- runny nose
- sneezing
- itching of the nose and throat
- itchy, watery eyes

WARNINGS SECTION

WARNINGS
Do not exceed recommended dosage

DO NOT USE IF PRINTED SAFETY SEAL IS MISSING OR BROKEN

- If you are now taking prescription monoamine oxidase inhibitor (MAOI) (certain drugs for depression, psychiatric, or emotional conditions or Parkinsons disease), or for 2 weeks after stopping the MAOI drug. If you do not know if your prescription drug contains an MAOI, ask a doctor or pharmacist before taking this product.

Ask a doctor before use if you have

- A cough that lasts or is chronic such as occurs with smoking, asthma, or emphysema
- A cough that occurs with too much phlegm (mucus)

Ask a doctor or pharmacist before us if you are:

- Taking sedatives or tranquilizers
- If you have a breathing problem such as emphysema or chronic bronchitis
- If you have glaucoma
- If you have difficult in urination due to enlargement of the prostate gland

OTC - WHEN USING SECTION

When using this product

- Excitability may occur, especially in children
- Marked drowsiness may occur
- Avoid alcoholic drinks
- Alcohol, sedatives, and tranquilizers may increase the drowsiness effect
- Be careful when driving a motor vehicle or operating machinery

OTC - DO NOT USE SECTION

Stop use and ask a doctor if

- Nervousness, dizziness, or sleeplessness occurs
- Symptoms do not improve within 7 days or are accompanied by a fever, rash, or persistent headache. A persistent cough may be a sign of a serious condition.
- New symptoms occur

OTC - PREGNANCY OR BREAST FEEDING SECTION

If pregnant or breast-feeding

Ask a health professional before use.

OTC - KEEP OUT OF REACH OF CHILDREN SECTION

Keep out of reach of children.
In case of overdose, get medical help or contact a Poison Control Center immediately.

Dosage and Administration

Directions

Do not exceed recommended dosage. Use calibrated measuring device for administering the drug to a child.

Adults and children 12 years of age and over: | 2 teaspoonfuls (10 ml) every 6 to 8 hours, not to exceed 6 teaspoonfuls in 24 hours, or as directed by a doctor.
Children 6 to under 12 years of age: | 1 teaspoonful (5 ml) every 6 to 8 hours, not to exceed 3 teaspoonfuls in 24 hours, or as directed by a doctor.
Children under 6 years of age: | Consult a doctor.

Other Information Store at 20° -25°C (68°-77°F); excursions permitted to 15°-30°C (59° - 86°F). [See USP Controlled Room Temperature].

INACTIVE INGREDIENT SECTION

Inactive Ingredients Citric Acid, Glycerin, Natural & Artificial Flavors, Propylene Glycol, Purified Water, Sodium Benzoate, Sodium Citrate, Sucralose

OTC - QUESTIONS SECTION

Questions? Comments?
To report a serious adverse event or obtain product information, contact 1-866-959-4880

PACKAGE LABEL.PRINCIPAL DISPLAY PANEL

23359-032-16

Ninjacof

Antitussive, Antihistamine

Each teaspoonful (5mL) Contains:

Chlophendianol HCl......................12.5mg

Pyrilamine Maleate.......................12.5mg

Alcohol Free Dye Free, Sugar Free

Cotton Candy Flavor

Centurion

16 fl oz (473 mL)

Manufactured for Centurion Labs, LLC Birmingham, AL 35243

Rev: 2/2015

EXP:

Lot:

23359-032-10

Ninjacof

Antitussive, Antihistamine

Each teaspoonful (5mL) Contains:

Chlophendianol HCl......................12.5mg

Pyrilamine Maleate.......................12.5mg

Alcohol Free Dye Free, Sugar Free

Cotton Candy Flavor

Centurion

16 fl oz (473 mL)

Manufactured for Centurion Labs, LLC Birmingham, AL 35243

Rev: 2/2015

EXP:

Lot:

23359-032-04

Ninjacof

Antitussive, Antihistamine

Each teaspoonful (5 mL) Contains:

Chlophendianol HCl......................12.5mg

Pyrilamine Maleate.......................12.5mg

Alcohol Free Dye Free, Sugar Free

Cotton Candy Flavor

Centurion

16 fl oz (473 mL)

Manufactured for Centurion Labs, LLC Birmingham, AL 35243

Rev: 2/2015

EXP:

Lot: